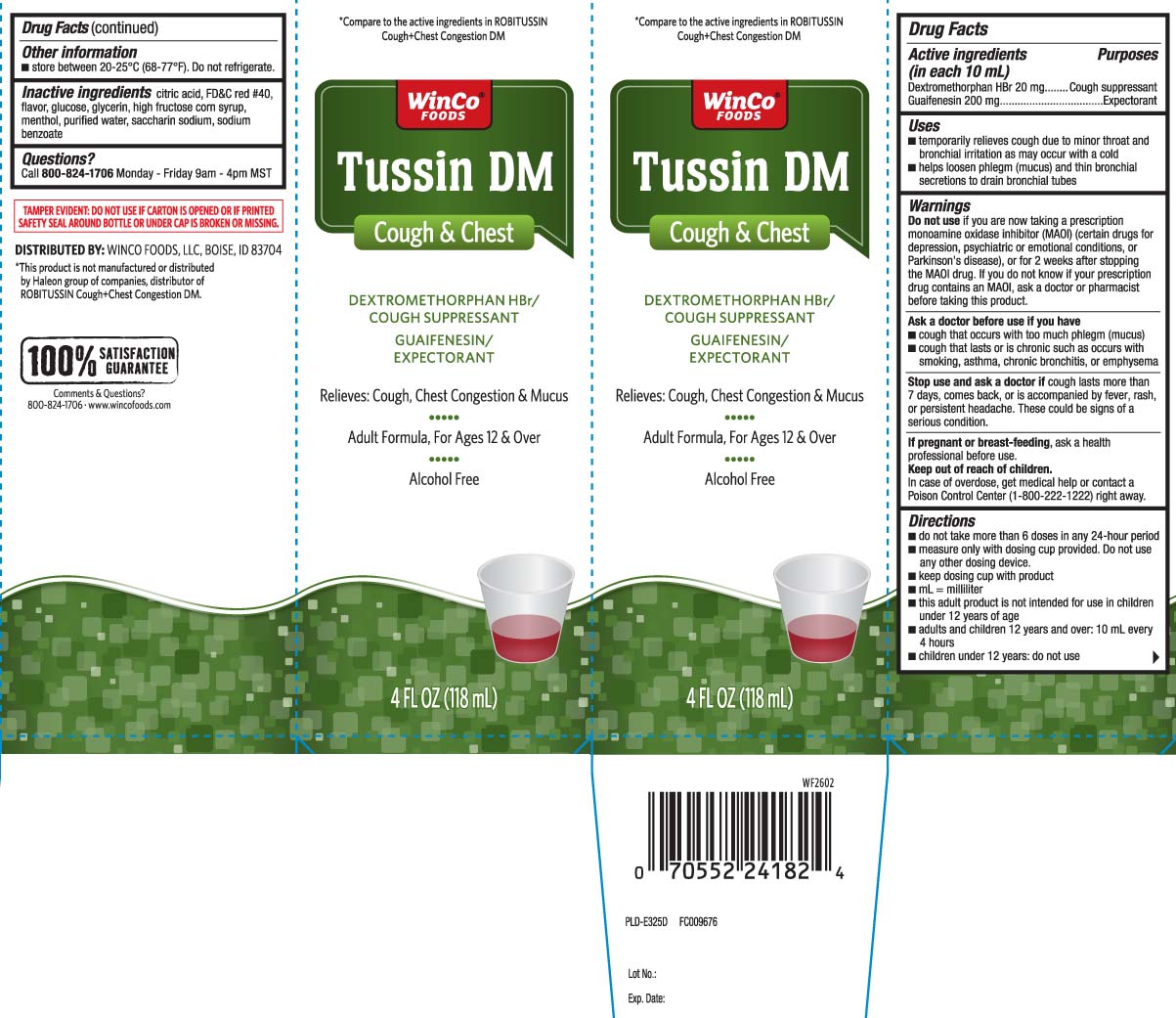 DRUG LABEL: Tussin DM Cough and Chest
NDC: 67091-469 | Form: LIQUID
Manufacturer: WinCo Foods, LLC
Category: otc | Type: HUMAN OTC DRUG LABEL
Date: 20260226

ACTIVE INGREDIENTS: DEXTROMETHORPHAN HYDROBROMIDE 20 mg/10 mL; GUAIFENESIN 200 mg/10 mL
INACTIVE INGREDIENTS: ANHYDROUS CITRIC ACID; FD&C RED NO. 40; DEXTROSE; GLYCERIN; HIGH FRUCTOSE CORN SYRUP; MENTHOL; WATER; SACCHARIN SODIUM; SODIUM BENZOATE

Drug Facts

Active ingredients (in each 10 mL)

Dextromethorphan HBr 20 mg

Guaifenesin, 200 mg

Purpose

Cough suppressant

Expectorant

Uses

- temporarily relieves cough due to minor throat and bronchial irritation as may occur with a cold
- helps loosen phlegm (mucus) and thin bronchial secretions to drain bronchial tubes

Warnings

Do not use

- if you are now taking a prescription monoamine oxidase inhibitor (MAOI) (certain drugs for depression, psychiatric or emotional conditions, or Parkinson’s disease), or for 2 weeks after stopping the MAOI drug. If you do not know if your prescription drug contains an MAOI, ask a doctor or pharmacist before taking this product.

Ask a doctor before use if you have

- cough that occurs with too much phlegm (mucus)
- cough that lasts or is chronic such as occurs with smoking, asthma, chronic bronchitis, or emphysema

Stop use and ask a doctor if

cough lasts more than 7 days, comes back, or is accompanied by fever, rash, or persistent headache. These could be signs of a serious condition.

If pregnant or breast-feeding,

ask a health professional before use.

Keep out of reach of children.

In case of overdose, get medical help or contact a Poison Control Center (1-800-222-1222) right away.

Directions

- do not take more than 6 doses in any 24-hour period
- measure only with dosing cup provided. Do not use any other dosing device.
- keep dosing cup with product
- mL = milliliter
- this adult product is not intended for use in children under 12 years of age
- adults and children 12 years and over: 10 mL every 4 hours
- children under 12 years:do not use

Other information

- store between 20-25ºC (68-77ºF). Do not refrigerate.

Inactive ingredients

anhydrous citric acid, FD&C red 40, flavor, glucose, glycerin, high fructose corn syrup, menthol, purified water, saccharin sodium, sodium benzoate

Questions?

Call 800-824-1706 Monday - Friday 9am - 4pm MST

Principal Display Panel

*Compare to the active ingredients in ROBITUSSIN® Cough + Chest Congestion DM

Tussin DM

Cough & Chest

DEXTROMETHORPHAN HBr/

COUGH SUPPRESSANT

GUAIFENESIN/

EXPECTORANT

Relieves: Cough, Chest Congestion & Mucus

Adult Formula, For Ages 12 & Over

Alcohol Free

FL OZ (mL)

*This product is not manufactured or distributed by Haleon group of companies,distributed of ROBITUSSIN Cough + Chest Congestion DM.

TAMPER EVIDENT: DO NOT USE IF CARTON IS OPENED OR IF PRINTED SAFETY SEAL AROUND BOTTLE OR UNDER CAP IS BROKEN OR MISSING.

DISTRIBUTED BY; WINCO FOODS, LLC, BOISE, ID 83704

www.wincofoods.com

Package Label

WINCO FOODS Cough & Chest Congestion DM